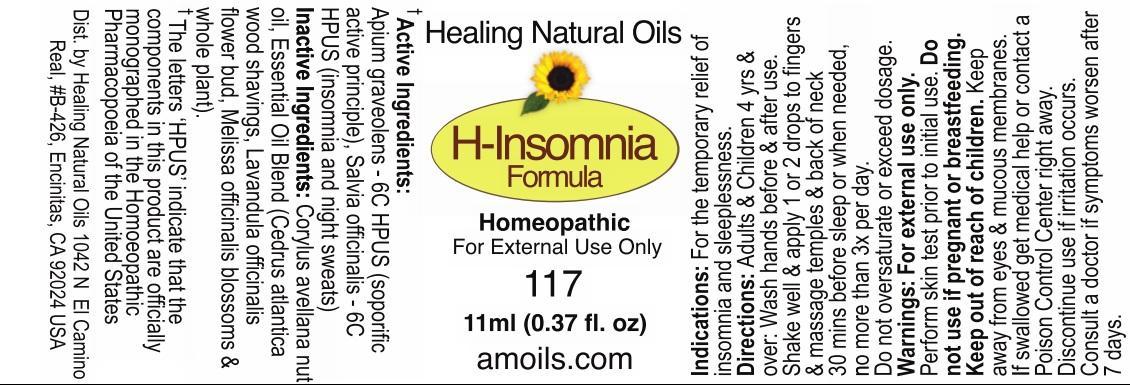 DRUG LABEL: H-Insomnia Formula
NDC: 61077-117 | Form: OIL
Manufacturer: Healing Natural Oils LLC
Category: homeopathic | Type: HUMAN OTC DRUG LABEL
Date: 20241211

ACTIVE INGREDIENTS: CELERY SEED 6 [hp_C]/11 mL; SAGE 6 [hp_C]/11 mL
INACTIVE INGREDIENTS: EUROPEAN HAZELNUT OIL; CEDRUS ATLANTICA BARK OIL; LAVANDULA ANGUSTIFOLIA FLOWERING TOP; MELISSA OFFICINALIS

Active Ingredients:

Apium graveolens - 6C HPUS
Salvia officinalis - 6C HPUS

Purpose

Apium graveolens - 6C HPUS (soporific active principle)
Salvia officinalis - 6C HPUS (insomnia and night sweats)
The letters ‘HPUS’ indicate that the components in this product are officially
monographed in the Homoeopathic Pharmacopoeia of the United States

Inactive Ingredients:

Corylus  avellana  nut  oil,  Essential  Oil  Blend  (Cedrus atlantica
wood shavings, Lavandula officinalis flower bud, Melissa officinalis blossoms and
whole plant).

Indications:

For the temporary relief of insomnia and sleeplessness.

Directions:

Adults and Children 4 yrs and over: Wash hands before and after use.
Shake well and apply 1 or 2 drops to fingers and massage temples and back of neck 30 mins before sleep or when needed, no more than 3x per day.
Do not oversaturate or exceed dosage.

Warnings:

For external use only.

Perform skin test prior to initial use.

Do not use if pregnant or breastfeeding.

Keep out of reach of children.

OTHER SAFETY INFORMATION

Keep away from eyes and mucous membranes. If swallowed get medical help
or contact a Poison Control Center right away.

Discontinue use if irritation occurs.

ASK DOCTOR

Consult a doctor if symptoms worsen after 7 days.

DESCRIPTION

Dist. by Healing Natural Oils 1042 N El Camino Real,

#B-426, Encinitas, CA 92024 USA

Principal Display Panel

Healing Natural Oils

H-Insomnia
Formula

Homeopathic

For External Use Only

117

11ml (0.37 fl. oz)
amoils.com